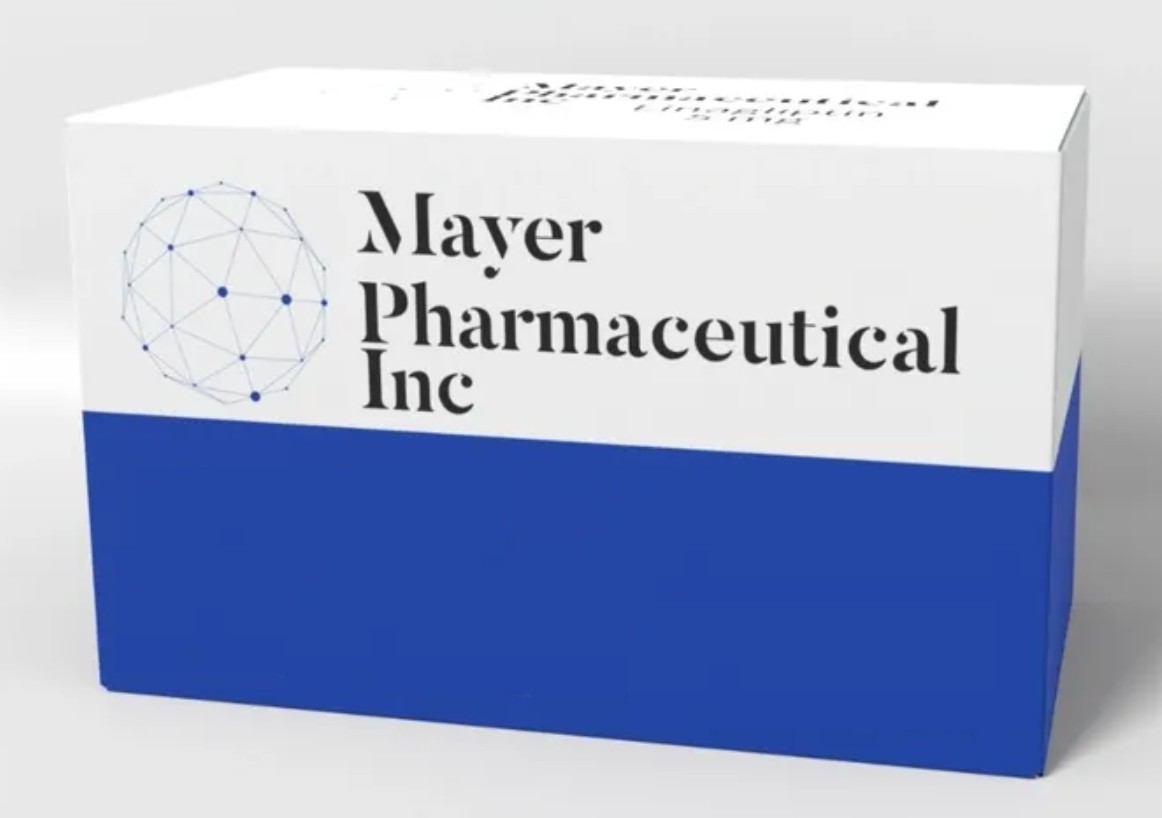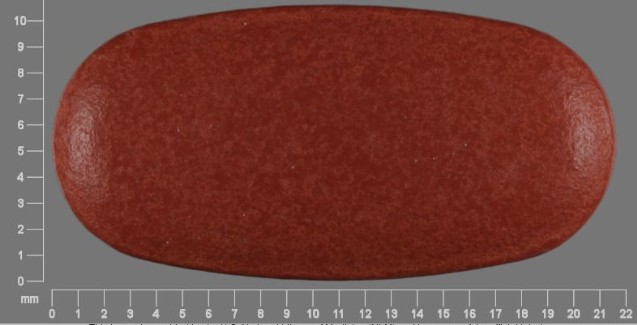 DRUG LABEL: SITAGLIPTIN - METFORMIN
NDC: 82922-100 | Form: TABLET
Manufacturer: Truemed Group LLC
Category: prescription | Type: HUMAN PRESCRIPTION DRUG LABEL
Date: 20230414

ACTIVE INGREDIENTS: METFORMIN 850 mg/1 1; SITAGLIPTIN 50 mg/1 1

SITAGLIPTIN - METFORMIN

CONTRAINDICATIONS

History of a serious hypersensitivity reaction to sitagliptin, such as anaphylaxis or angioedema. [See Warnings and Precautions (5.4); Adverse Reactions (6.2).]

PACKAGE LABEL

SITAGLIPTIN/METFORMIN 50/850MG